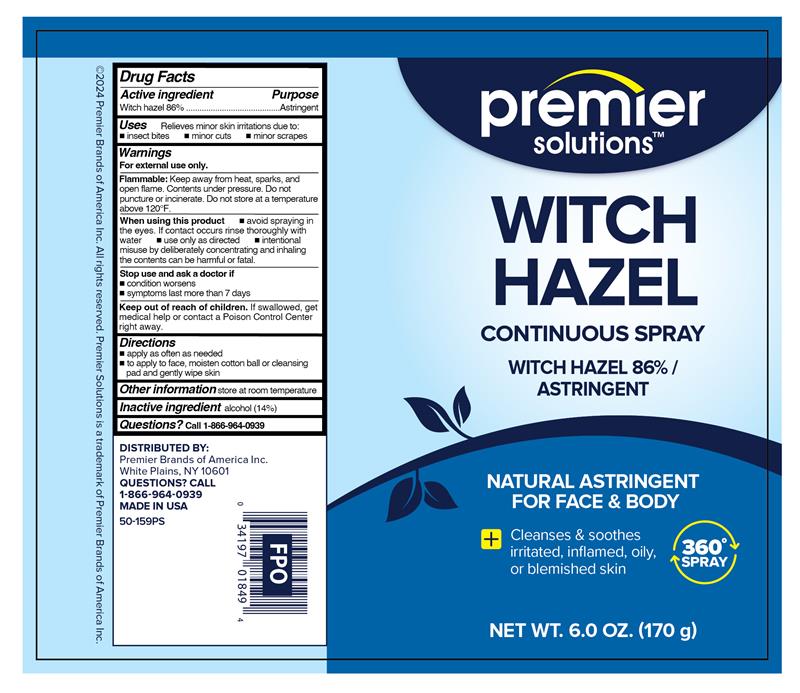 DRUG LABEL: Witch Hazel
NDC: 56104-904 | Form: SPRAY
Manufacturer: Premier Brands of America Inc.
Category: otc | Type: HUMAN OTC DRUG LABEL
Date: 20251103

ACTIVE INGREDIENTS: WITCH HAZEL 860 mg/1 g
INACTIVE INGREDIENTS: ALCOHOL

Premier Solutions Witch Hazel Spray

Active ingredient

Witch Hazel 86%

Purpose

Astringent

Uses

Relieves minor skin irritation due to:

- insect bites
- minor cuts
- minor scrapes

Warnings

For external use only.

Flammable:

Keep away from heat, sparks, and open flame. Contents under pressure. Do not puncture or incinerate. Do not store at a temperature above 120°F.

When using this product

- avoid spraying in the eyes. If contact occurs rinse thoroughly with water.
- use only as directed.
- intentional misuse by deliberately concentrating and inhaling the contents can be harful or fatal.

Stop use and ask a doctor if

- condition worsens
- symptoms persist for more than 7 days

Keep out of reach of children.

If swallowed, get medical help or contact a Poison Control Center right away.

Directions

- apply as often as needed
- to apply to face, moisten cotton ball or cleansing pad and gently wipe skin

Other information

store at room temperature

Inactive ingredient

alcohol (14%)

Questions?

Call 1-866-964-0939

RECENT MAJOR CHANGES

.

Principal Display Panel

premier

solutions

WITCH

HAZEL

CONTINUOUS SPRAY

WITCH HAZEL 86%/

ASTRINGENT

NATURAL ASTRINGENT

FOR FACE & BODY

Cleanses & soothes

irritated,inflamed, oily,

or blemished skin

NET WT. 6.0 0Z. (170 g)